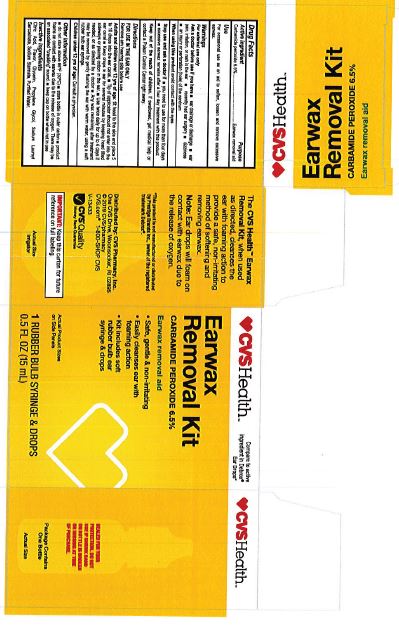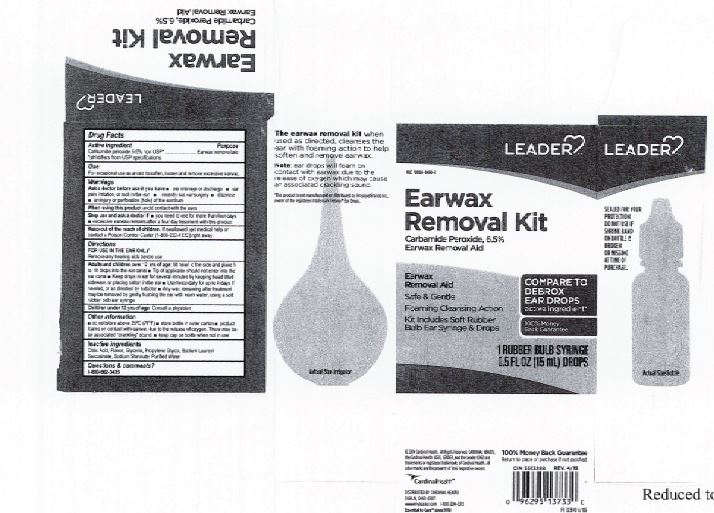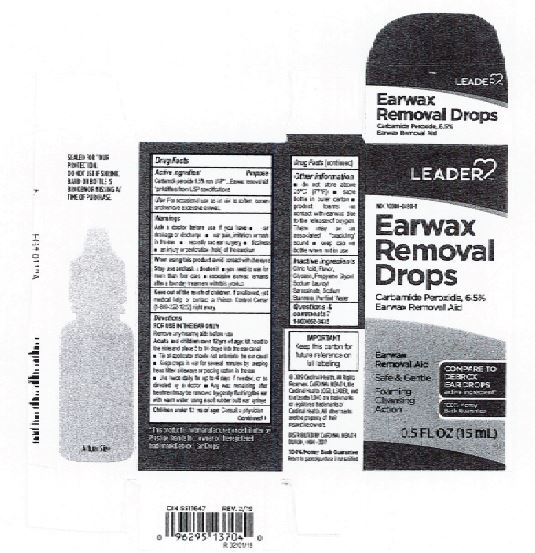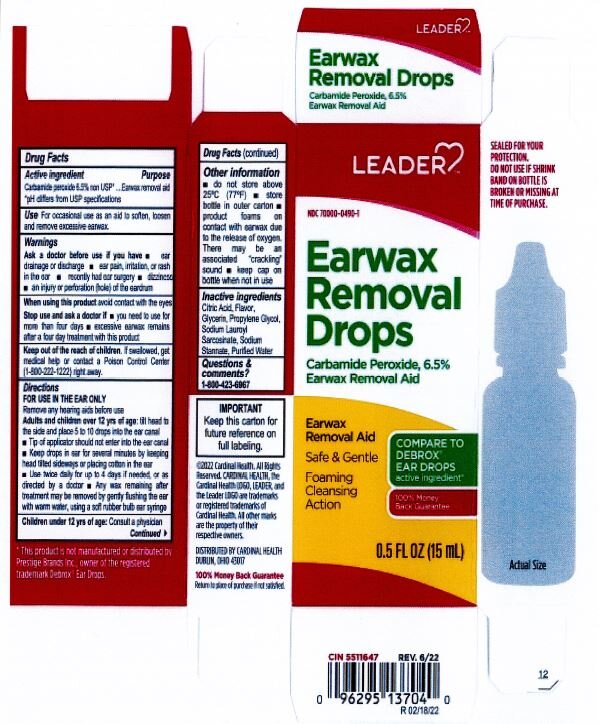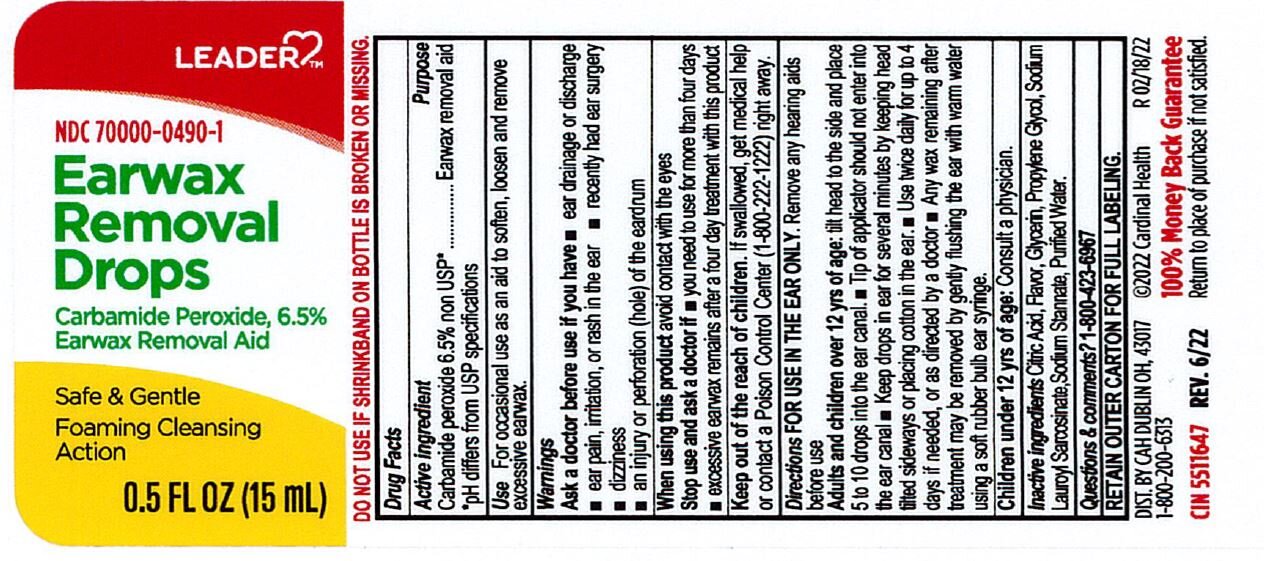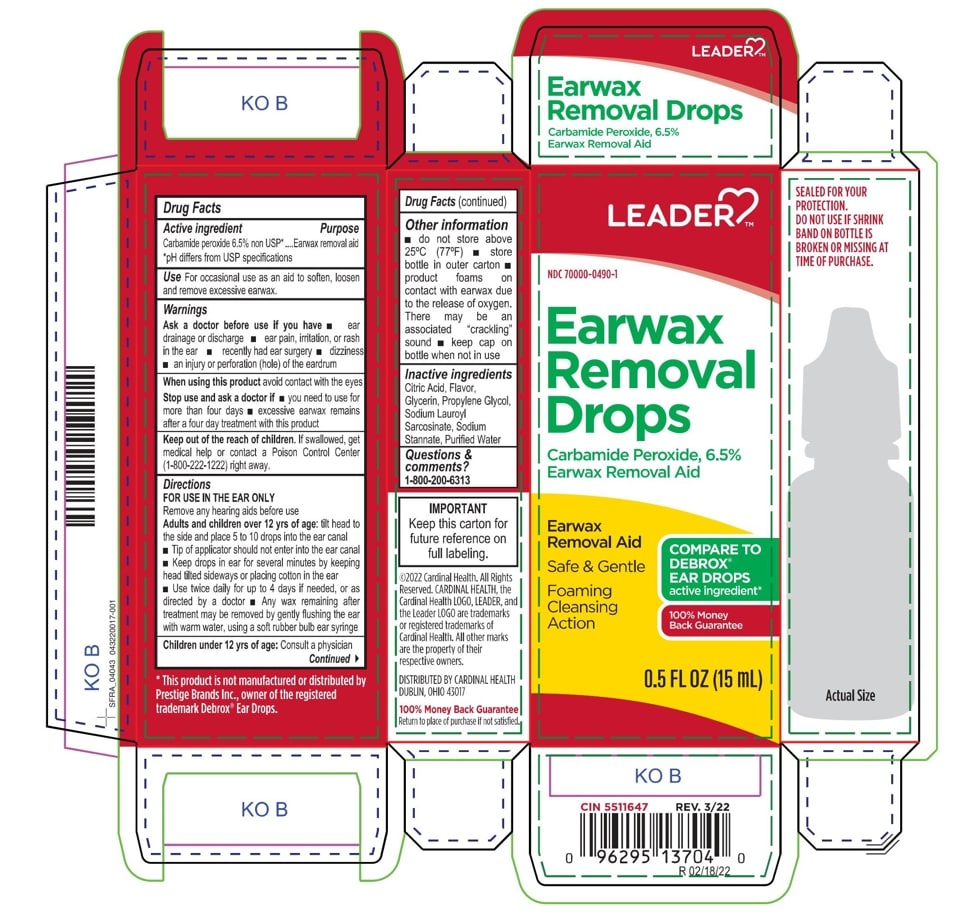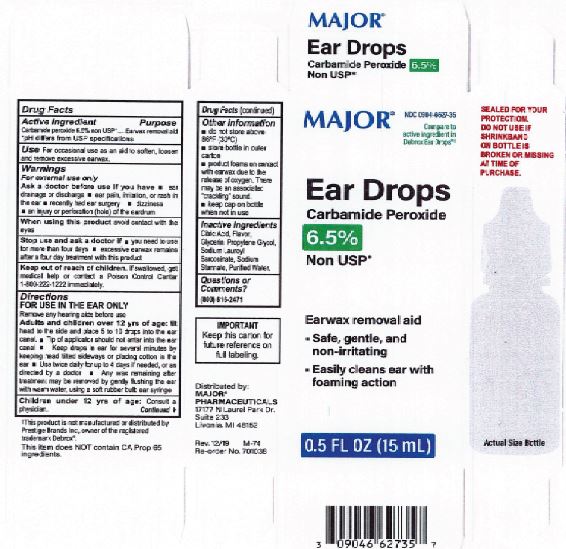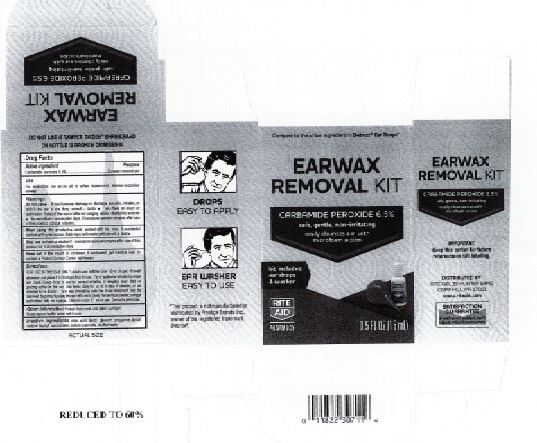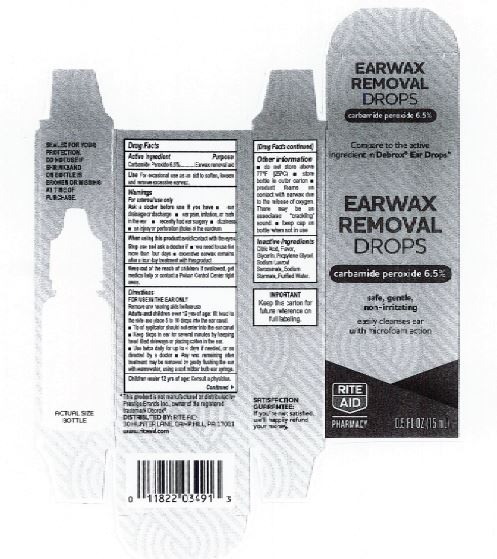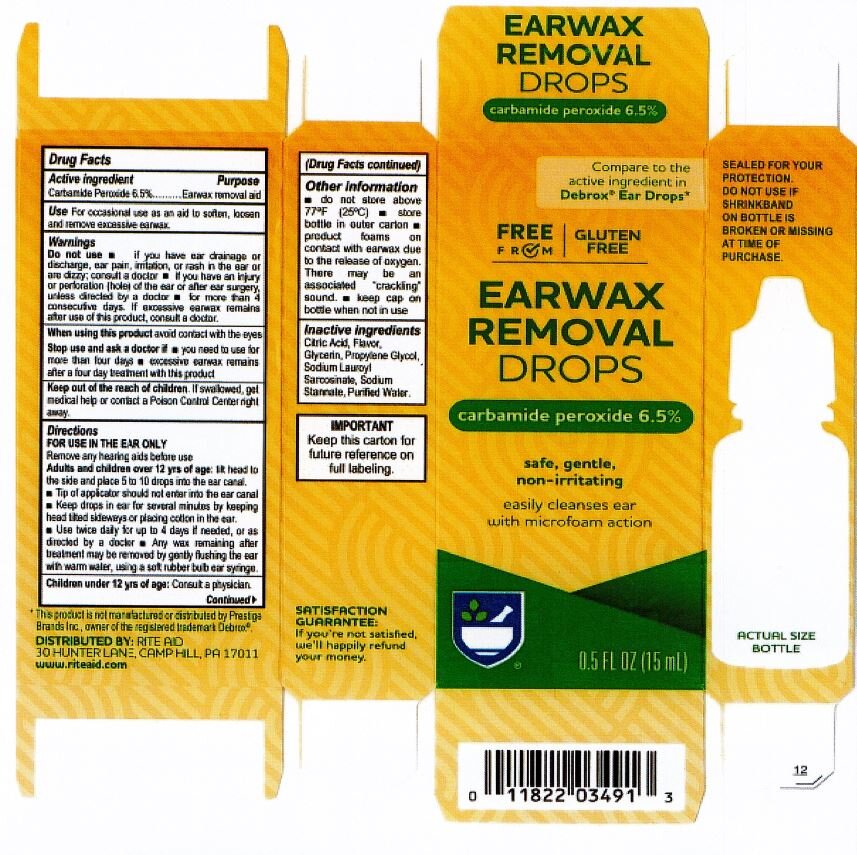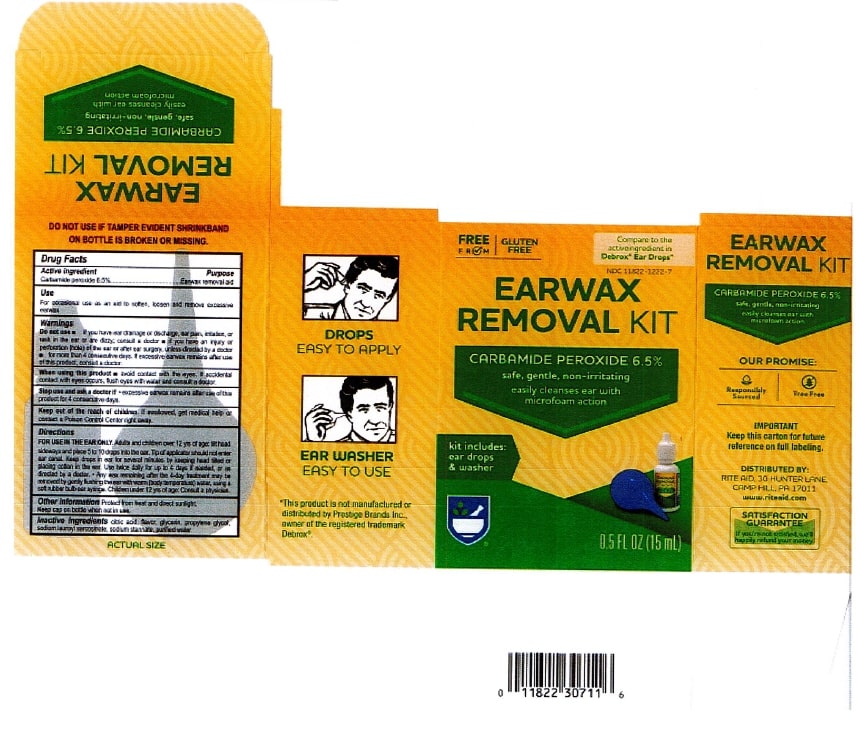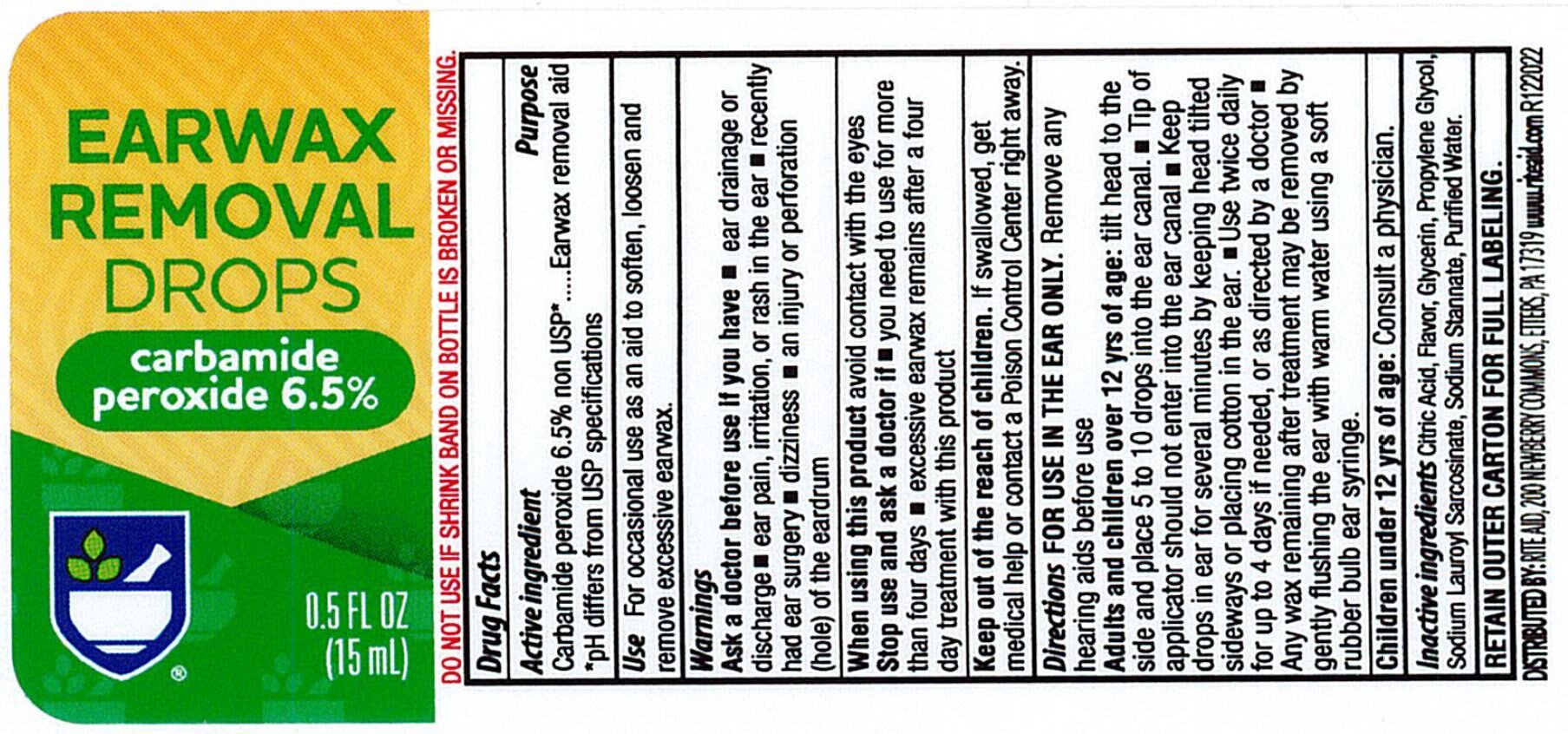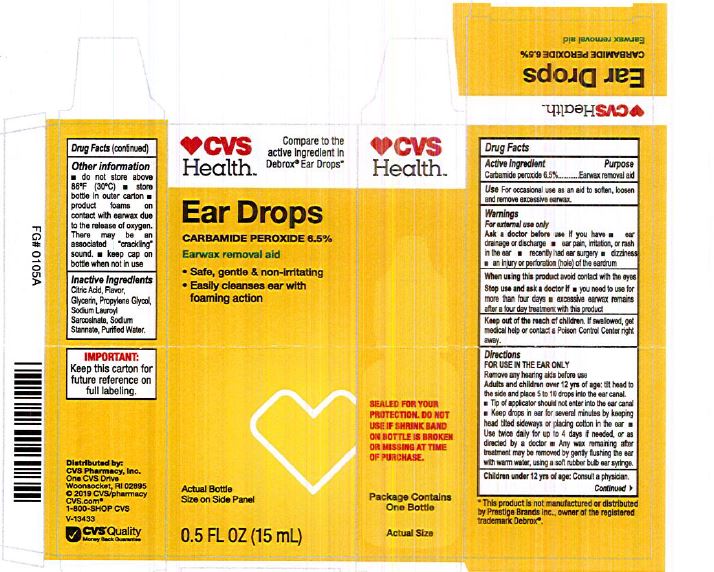 DRUG LABEL: Earwax Removal Drops
NDC: 82645-910 | Form: LIQUID
Manufacturer: Pharma Nobis, LLC
Category: otc | Type: HUMAN OTC DRUG LABEL
Date: 20231222

ACTIVE INGREDIENTS: CARBAMIDE PEROXIDE 0.065 mg/1 mL
INACTIVE INGREDIENTS: WATER; SODIUM STANNATE; SODIUM LAUROYL SARCOSINATE; ANHYDROUS CITRIC ACID; GLYCERIN; PROPYLENE GLYCOL

Private Label Earwax Removal- 0097

INACTIVE INGREDIENT

Citric Acid

Flavor

Glycerin

Propylene Glycol

Sodium Lauroyl Sarcosinate

Sodium Stannate

Purified Water

PURPOSE

Earwax removal aid.

DOSAGE AND ADMINISTRATION

Adults and children over 12 yrs of age: tilt head to the side and place 5 to 10 drops into the ear canal.

KEEP OUT OF REACH OF CHILDREN

Keep out of the reach of children. If swallowed, get medical help or contact a Poison Control Center right away.

WARNINGS

For External Use Only.

Ask a doctor before use if you have:

Ear drainage or discharge

Ear pain, irritation, or rash in the ear

Recently had ear surgery

Dizziness

An injury or perforation (hole) of the eadrum

ACTIVE INGREDIENT

Carbamide Peroxide 6.5%

INDICATIONS AND USAGE

For occasional use as an aid to soften, loosen and remove excessive earwax.